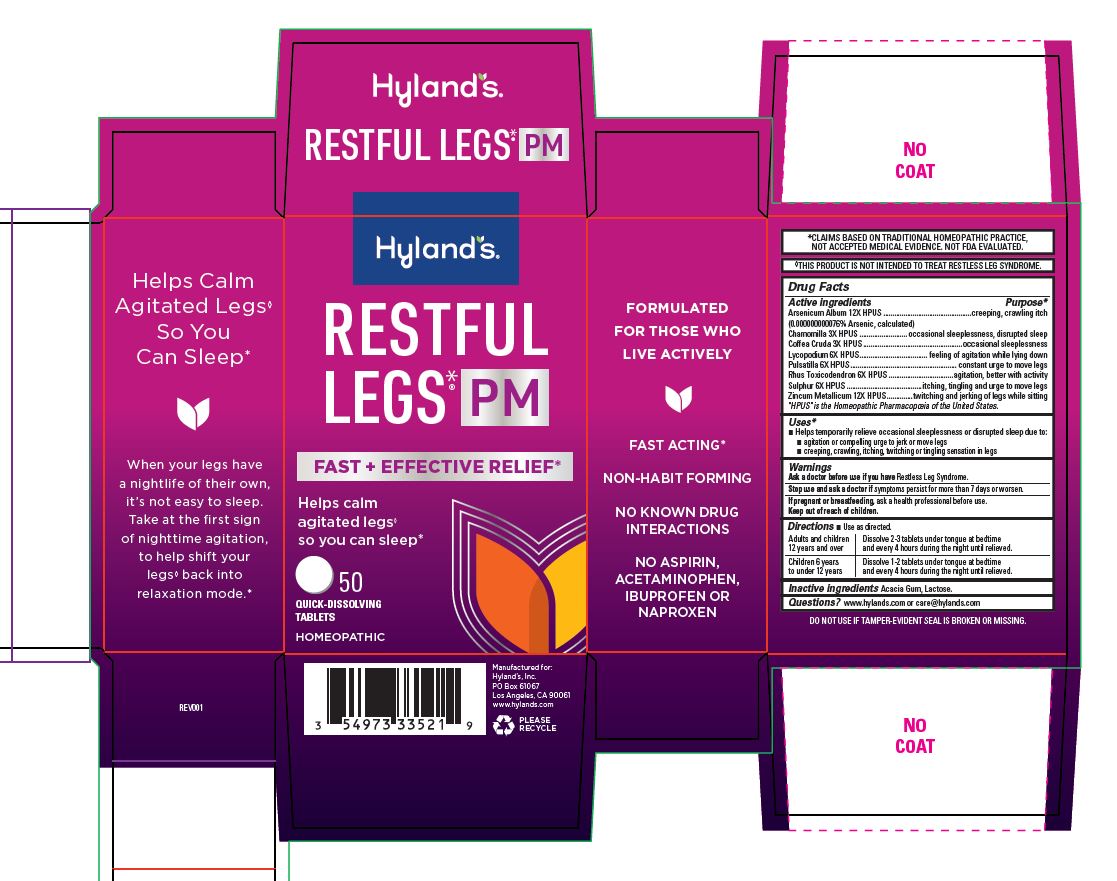 DRUG LABEL: Restful Legs PM
NDC: 54973-3352 | Form: TABLET
Manufacturer: Hyland's Inc.
Category: homeopathic | Type: HUMAN OTC DRUG LABEL
Date: 20250410

ACTIVE INGREDIENTS: ARSENIC TRIOXIDE 12 [hp_X]/1 1; MATRICARIA CHAMOMILLA 3 [hp_X]/1 1; SULFUR 6 [hp_X]/1 1; ZINC 12 [hp_X]/1 1; ARABICA COFFEE BEAN 3 [hp_X]/1 1; LYCOPODIUM CLAVATUM SPORE 6 [hp_X]/1 1; PULSATILLA PATENS WHOLE 6 [hp_X]/1 1; TOXICODENDRON PUBESCENS LEAF 6 [hp_X]/1 1
INACTIVE INGREDIENTS: ACACIA; LACTOSE MONOHYDRATE

Restful Legs PM

Drug Facts

Active Ingredients

Arsenicum Album 12X HPUS

Chamomilla 3X HPUS

Coffea Cruda 3X HPUS

Lycopodium 6X HPUS

Pulsatilla 6X HPUS

Rhus Toxicodendron 6X HPUS

Sulphur 6X HPUS

Zincum Metallicum 12X HPUS

“HPUS” indicates that the active ingredients are in the official Homeopathic Pharmacopœia of the United States.

Purpose

creeping, crawling itch

occasional sleeplessness, disrupted sleep

occasional sleeplessness

feeling of agitation while lying down

constant urge to move legs

agitation, better with activity

itching, tingling, and urge to move legs

twitching and jerking of legs while sitting

Uses

■ Helps temporarily relieve occasional sleeplessness or disrupted sleep due to:

■ agitation or compelling urge to jerk or move legs

■ itching, tingling, or crawling sensations in legs

Warnings

Ask a doctor before use if you have

Restless Leg Syndrome.

Stop use and ask a doctor if

symptoms persist for more than 7 days or worsen.

If pregnant or breastfeeding

Ask a health professional before use

Directions

■ Use as directed.

Adults and Children; 12 years and over | Dissolve 2-3 tablets under tongue at bedtime and; every 4 hours during the night until relieved.
Children 6 years; to under 12 years | Dissolve 1-2 tablets under tongue at bedtime and; every 4 hours during the night until relieved.

Inactive Ingredients

Acacia Gum, Lactose.

Questions?

www.hylands.com or care@hylands.com

Indications and Usage

Added bullets

Updated to

■ Helps temporarily relieve occasional sleeplessness or disrupted sleep due to:

■ agitation or compelling urge to jerk or move legs

■ itching, tingling, or crawling sensations in legs

Principal Display Panel- Restful Legs PM 50 Count

Hyland's

NATURALS™

RESTFUL

LEGS PM

FAST + EFFECTIVE RELIEF*

Helps calm

agitated legs

so you can sleep**

50

QUICK-DISSOLVING

TABLETS

HOMEOPATHIC